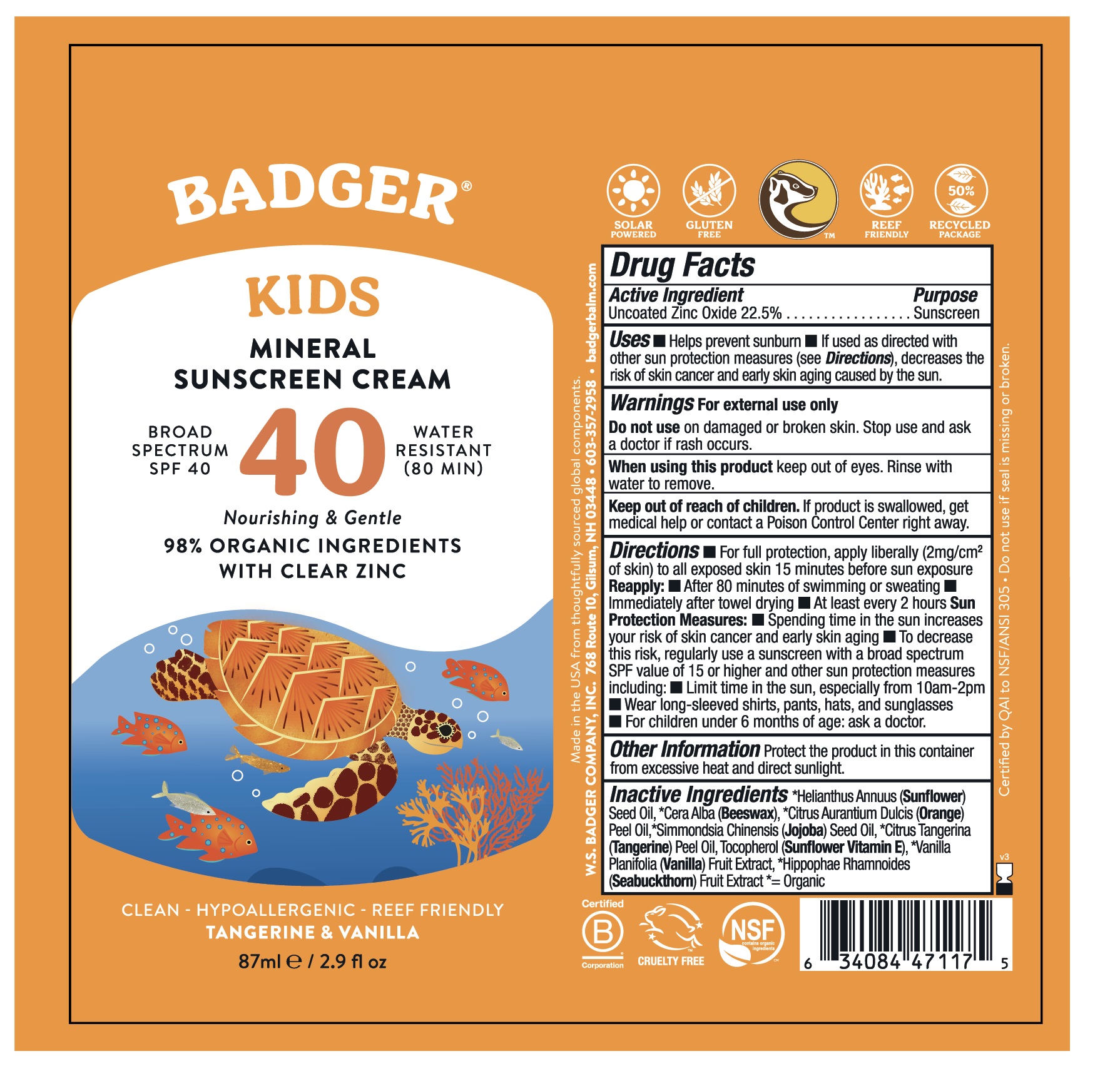 DRUG LABEL: Badger Kids Mineral Sunscreen Cream Broad Spectrum SPF 40
NDC: 62206-4021 | Form: CREAM
Manufacturer: W.S. Badger Company, Inc.
Category: otc | Type: HUMAN OTC DRUG LABEL
Date: 20241231

ACTIVE INGREDIENTS: ZINC OXIDE 22.5 g/100 mL
INACTIVE INGREDIENTS: SUNFLOWER OIL; YELLOW WAX; TOCOPHEROL; HIPPOPHAE RHAMNOIDES FRUIT; ORANGE OIL; MANDARIN OIL; VANILLA; JOJOBA OIL

Badger® Kids Mineral Sunscreen Broad Spectrum SPF 40 Cream

Drug Facts

Active Ingredient

Non-Nano Uncoated Zinc Oxide 22.5%

Purpose

Sunscreen

Uses

- Helps prevent sunburn
- If used as directed with other sun protection measures (see Directions), decreases the risk of skin cancer and early skin aging caused by the sun.

Warnings

For external use only

Do not use on damaged or broken skin. Stop and ask a doctor if rash occurs.

When using this product keep out of eyes. Rinse with water to remove.

Keep out of reach of children. If product is swallowed, get medical help or contact a Poison Control Center right away.

Directions

- For full protection, apply liberally (2mg/cm^2 of skin) to all exposed skin 15 minutes before sun exposure, then rub in to reduce whitening effect.

Reapply:

- After 80 minutes of swimming or sweating
- Immediately after towel drying
- At least every 2 hours

Sun Protection Measures:

- Spending time in the sun increases your risk of skin cancer and early skin aging
- To decrease this risk, regularly use a sunscreen with a broad spectrum SPF value of 15 or higher and other sun protection measures including:
  - Limit time in the sun, especially from 10am-2pm
  - Wear long-sleeved shirts, pants, hats, and sunglasses
- For children under 6 months of age: ask a doctor.

Inactive Ingredients

Helianthus Annuus (Sunflower) Seed Oil,*Cera Alba (Beeswax),*Citrus Aurantium Dulcis (Orange) Peel Oil, *Simmondsia Chinensis (Jojoba) Seed Oil,*Citrus Tangerina (Tangerine) Peel Oil, Tocopherol (Sunflower Vitamin E), *Vanilla Planifolia (Vanilla),*Hippophae Rhamnoides (Seabuckthorn).

*= Organic

Other Information

Protect the product in this container from excessive heat and direct sunlight.

PRINCIPAL DISPLAY PANEL - 87 mL Tube Label

BADGER ®

Kids Mineral Sunscreen Cream

Tangerine & Vanilla

Broad Spectrum SPF 40

NATURAL MINERALS
Clean • Hypoallergenic • Reef Friendly

WATER RESISTANT 80 min

CLEAR ZINC

Solar Powered

Gluten Free

Reef Friendly

Recycled Package

Cruelty Free

Certified B Corps

98% ORGANIC INGREDIENTS & CLEAR ZINC OXIDE

87ml/2.9 fl.oz